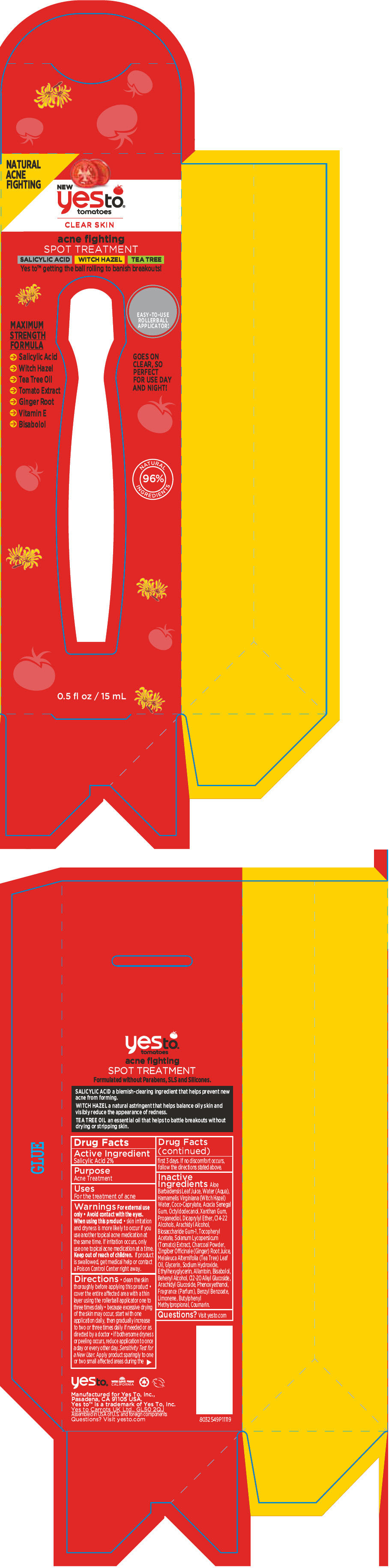 DRUG LABEL: Yes To Tomatoes Acne Fighting Spot Treatment
NDC: 69840-014 | Form: LIQUID
Manufacturer: Yes To, Inc.
Category: otc | Type: HUMAN OTC DRUG LABEL
Date: 20190429

ACTIVE INGREDIENTS: SALICYLIC ACID 20 mg/1 mL
INACTIVE INGREDIENTS: ALOE VERA LEAF; WATER; HAMAMELIS VIRGINIANA TOP WATER; PROPANEDIOL; ALLANTOIN; GLYCERIN; ACTIVATED CHARCOAL; SOLANUM LYCOPERSICUM; TEA TREE OIL; COCO-CAPRYLATE/CAPRATE; ACACIA; OCTYLDODECANOL; XANTHAN GUM; DICAPRYLYL ETHER; C14-22 ALCOHOLS; ARACHIDYL ALCOHOL; BIOSACCHARIDE GUM-1; PHENOXYETHANOL; DOCOSANOL; C12-20 ALKYL GLUCOSIDE; ARACHIDYL GLUCOSIDE; .ALPHA.-TOCOPHEROL ACETATE, DL-; SODIUM HYDROXIDE; ETHYLHEXYLGLYCERIN; .ALPHA.-BISABOLOL, (+/-)-; GINGER

Yes To® Tomatoes Acne Fighting Spot Treatment

Drug Facts

Active Ingredient

Salicylic Acid 2%

Purpose

Acne Treatment

Uses

For the treatment of acne

Warnings

For external use only

- Avoid contact with the eyes.

When using this product

- skin irritation and dryness is more likely to occur if you use another topical acne medication at the same time. If irritation occurs, only use one topical acne medication at a time.

Keep out of reach of children. If product is swallowed, get medical help or contact a Poison Control Center right away.

Directions

- clean the skin thoroughly before applying this product
- cover the entire affected area with a thin layer using the rollerball applicator one to three times daily
- because excessive drying of the skin may occur, start with one application daily, then gradually increase to two or three times daily if needed or as directed by a doctor
- if bothersome dryness or peeling occurs, reduce application to once a day or every other day.

Sensitivity Test for a New User

Apply product sparingly to one or two small affected areas during the first 3 days. If no discomfort occurs, follow the directions stated above.

Inactive Ingredients

Aloe Barbadensis Leaf Juice, Water (Aqua), Hamamelis Virginiana (Witch Hazel) Water, Coco-Caprylate, Acacia Senegal Gum, Octyldodecanol, Xanthan Gum, Propanediol, Dicaprylyl Ether, C14-22 Alcohols, Arachidyl Alcohol, Biosaccharide Gum-1, Tocopheryl Acetate, Solanum Lycopersicum (Tomato) Extract, Charcoal Powder, Zingiber Officinale (Ginger) Root Juice, Melaleuca Alternifolia (Tea Tree) Leaf Oil, Glycerin, Sodium Hydroxide, Ethylhexyglycerin, Allantoin, Bisabolol, Behenyl Alcohol, C12-20 Alkyl Glucoside, Arachidyl Glucoside, Phenoxyethanol, Fragrance (Parfum), Benzyl Benzoate, Limonene, Butylphenyl Methylpropional, Coumarin.

Questions?

Visit yesto.com

PRINCIPAL DISPLAY PANEL - 15 mL Bottle Box

NATURAL
ACNE
FIGHTING

NEW
yesto®
tomatoes

CLEAR SKIN

acne fighting
SPOT TREATMENT

SALICYLIC ACID
WITCH HAZEL
TEA TREE

Yes to™ getting the ball rolling to banish breakouts!

MAXIMUM
STRENGTH
FORMULA

→ Salicylic Acid
→ Witch Hazel
→ Tea Tree Oil
→ Tomato Extract
→ Ginger Root
→ Vitamin E
→ Bisabolol

EASY-TO-USE
ROLLERBALL
APPLICATOR!

GOES ON
CLEAR, SO
PERFECT
FOR USE DAY
AND NIGHT!

NATURAL
96%
INGREDIENTS

0.5 fl oz / 15 mL